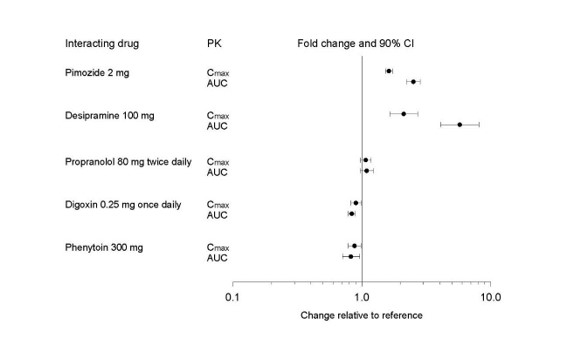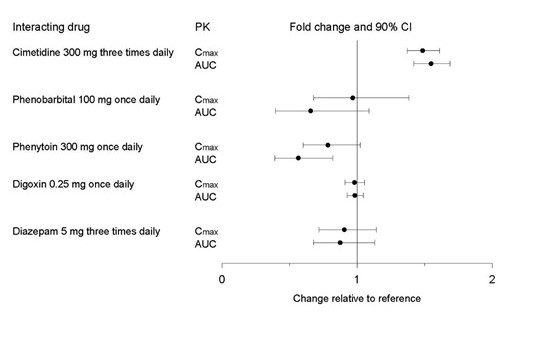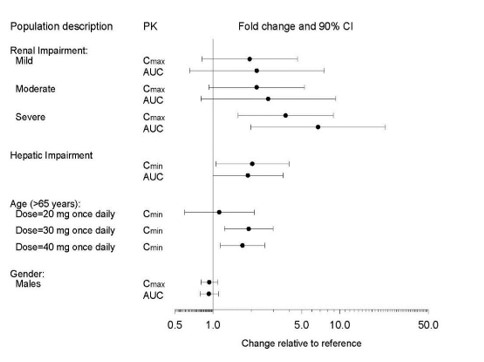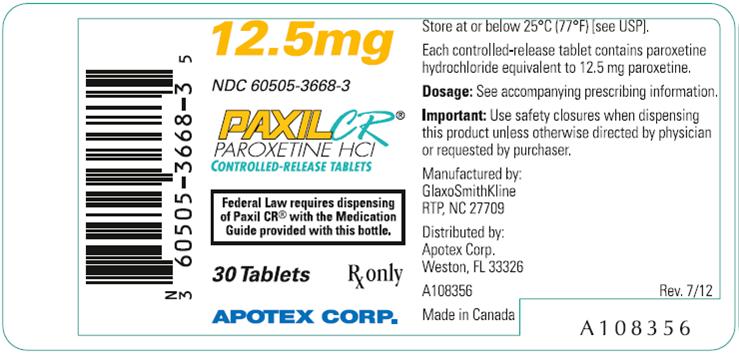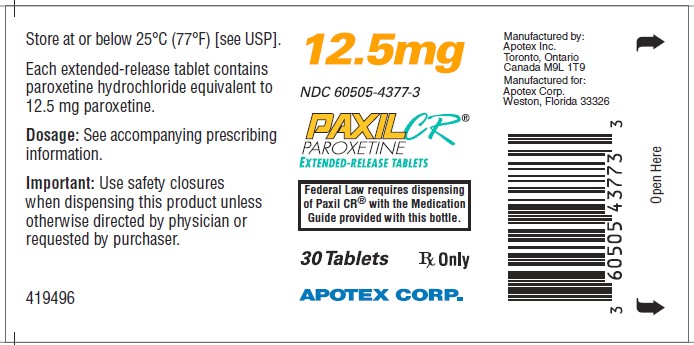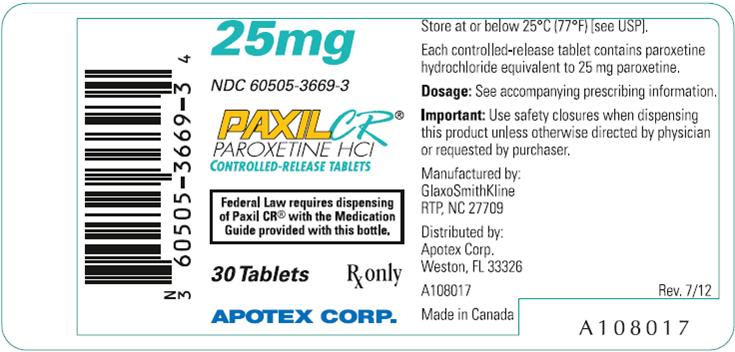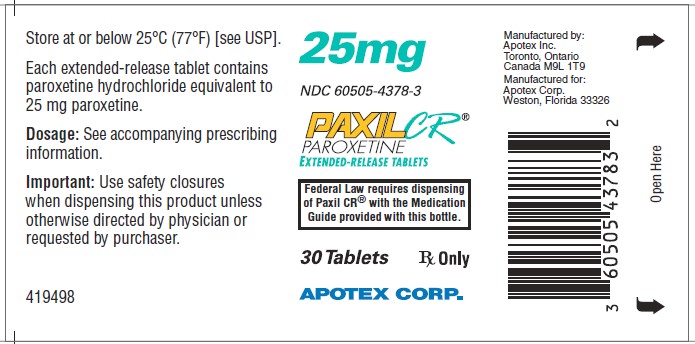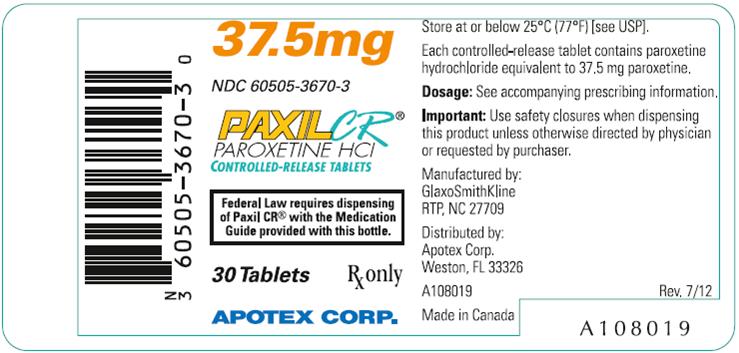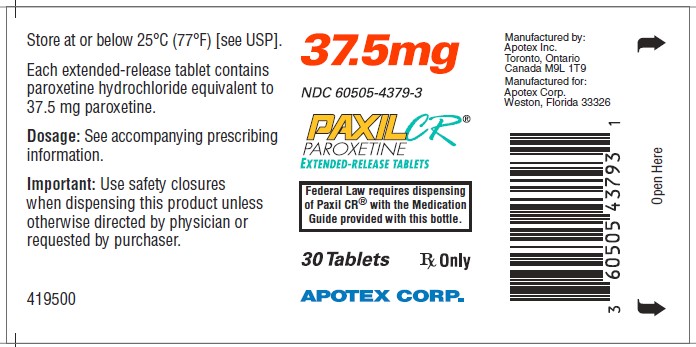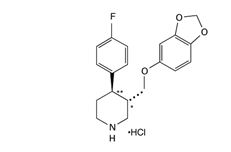 DRUG LABEL: PAXIL 
NDC: 60505-4377 | Form: TABLET, FILM COATED, EXTENDED RELEASE
Manufacturer: Apotex Corp
Category: prescription | Type: HUMAN PRESCRIPTION DRUG LABEL
Date: 20250922

ACTIVE INGREDIENTS: PAROXETINE HYDROCHLORIDE 12.5 mg/1 1
INACTIVE INGREDIENTS: HYPROMELLOSE, UNSPECIFIED; POVIDONE K30; LACTOSE MONOHYDRATE; MAGNESIUM STEARATE; SILICON DIOXIDE; GLYCERYL DIBEHENATE; METHACRYLIC ACID AND ETHYL ACRYLATE COPOLYMER; SODIUM LAURYL SULFATE; POLYSORBATE 80; TALC; TRIETHYL CITRATE; TITANIUM DIOXIDE; POLYETHYLENE GLYCOL 10000; D&C YELLOW NO. 10; FD&C YELLOW NO. 6 ; FERRIC OXIDE YELLOW   

HIGHLIGHTS OF PRESCRIBING INFORMATION

These highlights do not include all the information needed to use PAXIL CR safely and effectively. See full prescribing information for PAXIL CR.
PAXIL CR (paroxetine) extended-release Tablets, for oral use
Initial U.S. Approval: 1992

RECENT MAJOR CHANGES

Warnings and Precautions (5.2, 5.4, 5.5) 8/2023

WARNING: SUICIDAL THOUGHTS AND BEHAVIORS

See full prescribing information for complete boxed warning.

Increased risk of suicidal thoughts and behavior in pediatric and young adult patients taking antidepressants. Closely monitor all antidepressant-treated patients for clinical worsening and emergence of suicidal thoughts and behaviors. PAXIL CR is not approved for use in pediatric patients. (5.1, 8.4)

1 INDICATIONS AND USAGE

PAXIL CR is a selective serotonin reuptake inhibitor (SSRI) indicated for use in adults for the treatment of (1):

- Major Depressive Disorder (MDD)
- Panic Disorder (PD)
- Social Anxiety Disorder (SAD)
- Premenstrual Dysphoric Disorder (PMDD)

2 DOSAGE AND ADMINISTRATION

- Swallow tablet whole; do not chew or crush. (2.1)
- Recommended starting and maximum daily dosage: (2.2, 2.3)

Indication | Starting Dose | Maximum Dose
MDD | 25 mg/day | 62.5 mg/day
PD | 12.5 mg/day | 75 mg/day
SAD | 12.5 mg/day | 37.5 mg/day
PMDD | 12.5 mg/day | 25 mg/day

- For PMDD, dose continuously or intermittently (luteal phase only). (2.3)
- If inadequate response to starting dosage, titrate in 12.5 mg per day increments once weekly. (2.2, 2.3)
- Elderly patients, patients with severe renal impairment or severe hepatic impairment: Starting dose is 12.5 mg per day. Do not exceed 50 mg per day for treatment of MDD and PD and 37.5 mg per day for treatment of SAD. (2.5)
- When discontinuing PAXIL CR, reduce dose gradually. (2.7)

3 DOSAGE FORMS AND STRENGTHS

Extended-release tablets:12.5 mg, 25 mg, and 37.5 mg tablets. (3)

4 CONTRAINDICATIONS

- Concomitant use of monoamine oxidase inhibitors (MAOIs) or use within 14 days of discontinuing a MAOIs. (4, 5.2, 7)
- Concomitant use of pimozide or thioridazine. (4, 5.3, 7)
- Known hypersensitivity to paroxetine or to any of the inactive ingredients in PAXIL CR. (4)

5 WARNINGS AND PRECAUTIONS

- Serotonin Syndrome: Increased risk when co-administered with other serotonergic agents, but also when taken alone. If occurs, discontinue PAXIL CR and serotonergic agents and initiate supportive measures. (5.2)
- Embryofetal Toxicity: May cause fetal harm.Meta-analysis of epidemiological studies have shown increased risk (less than 2-fold) of cardiovascular malformations with exposure during the first trimester. (5.4, 8.1)
- Increased Risk of Bleeding: Concomitant use of aspirin, nonsteroidal anti-inflammatory drugs, other antiplatelet drugs, warfarin, and other anticoagulant drugs may increase risk. (5.5)
- Activation of Mania/Hypomania: Screen patients for bipolar disorder. (5.6)
- Seizures: Use with caution in patients with seizure disorders. (5.8)
- Angle-Closure Glaucoma: Angle-closure glaucoma has occurred in patients with untreated anatomically narrow angles, treated with antidepressants (5.9)
- Sexual Dysfunction: PAXIL CR may cause symptoms of sexual dysfunction. (5.13)

6 ADVERSE REACTIONS

Most common adverse reactions (≥5% and at least twice placebo) in placebo-controlled MDD, PD, SAD, and PMDD clinical trials:

abnormal ejaculation, abnormal vision, asthenia, constipation, decreased appetite, diarrhea, dizziness, dry mouth, female genital disorder, impotence, insomnia, libido decreased, nausea, somnolence, sweating, tremor. (6.1)

To report SUSPECTED ADVERSE REACTIONS, contact Apotex Corp.at 1-800-706-5575 or FDA at 1-800-FDA-1088 or www.fda.gov/medwatch.

7 DRUG INTERACTIONS

- Drugs Highly Bound to Plasma Protein: Monitor for adverse reactions and reduce dosage of PAXIL CR or other protein-bound drugs (e.g., warfarin) as warranted. (7)
- Drugs Metabolized by CYP2D6: Reduce dosage of drugs metabolized by CYP2D6 as warranted. (7)
- Concomitant use with Tamoxifen: Consider use of an alternative antidepressant with little or no CYP2D6 inhibition. (5.11, 7)

8 USE IN SPECIFIC POPULATIONS

- Pregnancy: SSRI use, particularly later in pregnancy, may increase the risk of persistent pulmonary hypertension and symptoms of poor adaptation (respiratory distress, temperature instability, feeding difficulty, hypotonia, irritability) in the neonate. (5.4, 8.1)
- Nursing Mothers: Discontinue drug or nursing taking into consideration importance of drug to mother. (8.3)

FULL PRESCRIBING INFORMATION

WARNING: SUICIDAL THOUGHTS AND BEHAVIORS

Antidepressants increased the risk of suicidal thoughts and behaviors in pediatric and young adult patients in short-term studies. Closely monitor all antidepressant-treated patients for clinical worsening, and for emergence of suicidal thoughts and behaviors [See Warnings and Precautions (5.1)] PAXIL CR is not approved for use in pediatric patients [see Use in Specific Populations (8.4)].

1 INDICATIONS AND USAGE

PAXIL CR is indicated in adults for the treatment of:

- Major depressive disorder (MDD)
- Panic disorder (PD)
- Social anxiety disorder (SAD)
- Premenstrual dysphoric disorder (PMDD)

2 DOSAGE AND ADMINISTRATION

2.1 Important Administration Instructions

Administer PAXIL CR as a single daily dose in the morning, with or without food. Swallow tablets whole and do not chew or crush.

2.2 Dosage in Patients with Major Depressive Disorder, Panic Disorder, and Social Anxiety Disorder

The recommended initial dosage and maximum dosage of PAXIL CR in patients with MDD, PD, and SAD are presented in Table 1.

In patients with an inadequate response, dosage may be increased in increments of 12.5 mg per day at intervals of at least 1 week, depending on tolerability.

Table 1: Recommended Daily Dosage of PAXIL CR in Patients with MDD, PD, and SAD

Indication | Starting Dose | Maximum Dose
MDD | 25 mg | 62.5 mg
PD | 12.5 mg | 75 mg
SAD | 12.5 mg | 37.5 mg

2.3 Dosage in Patients with Premenstrual Dysphoric Disorder

The recommended starting dosage in women with PMDD is 12.5 mg per day. PAXIL CR may be administered either continuously (every day throughout the menstrual cycle) or intermittently (only during the luteal phase of the menstrual cycle, i.e., starting the daily dosage 14 days prior to the anticipated onset of menstruation and continuing through the onset of menses). Intermittent dosing is repeated with each new cycle.

In patients with an inadequate response, the dosage may be increased to the maximum recommended dosage of 25 mg per day, depending on tolerability. Institute dosage adjustments at intervals of at least 1 week.

2.4 Screen for Bipolar Disorder Prior to Starting Paxil CR

Prior to initiating treatment with Paxil CR or another antidepressant, screen patients for a personal or family history of bipolar disorder, mania, or hypomania [see Warnings and Precautions (5.6)].

2.5 Dosage Modifications for Elderly Patients, Patients with Severe Renal Impairment and Patients with Severe Hepatic Impairment

The recommended initial dose of PAXIL CR is 12.5 mg per day for elderly patients, patients with severe renal impairment, and patients with severe hepatic impairment. Reduce initial dose and increase up-titration intervals if necessary. Dosage should not exceed 50 mg per day for MDD or PD and should not exceed 37.5 mg per day for SAD [see Use in Specific Populations (8.5, 8.6)].

2.6 Switching Patients to or from a Monoamine Oxidase Inhibitor Antidepressant

At least 14 days must elapse between discontinuation of an monoamine oxidase inhibitor (MAOI) antidepressant and initiation of PAXIL CR. In addition, at least 14 days must elapse after stopping PAXIL CR before starting an MAOI antidepressant [see Contraindications (4), Warnings and Precautions (5.2)].

2.7 Discontinuation of Treatment with Paxil CR

Adverse reactions may occur upon discontinuation of PAXIL CR [see Warnings and Precautions (5.7)]. Gradually reduce the dosage rather than stopping Paxil CR abruptly whenever possible.

3 DOSAGE FORMS AND STRENGTHS

PAXIL CR is supplied as a round extended-release tablet as follows:

12.5-mg yellow, round tablets, (One face is plain and the other is engraved with "12.5")

25-mg pink, round tablets, (One face is plain and the other is engraved with "25")

37.5 mg blue, round tablets, (One face is plain and the other is engraved with "37.5")

4 CONTRAINDICATIONS

PAXIL CR is contraindicated in patients:

- Taking, or within 14 days of stopping, MAOIs (including the MAOIs linezolid and intravenous methylene blue) because of an increased risk of serotonin syndrome [See Warnings and Precautions (5.2), Drug Interactions (7)].
- Taking thioridazine because of risk of QT prolongation [see Warnings and Precautions (5.3), Drug Interactions (7)].
- Taking pimozide because of risk of QT prolongation [see Warnings and Precautions (5.3), Drug Interactions (7)].
- With known hypersensitivity (e.g., anaphylaxis, angioedema, Stevens-Johnson syndrome) to paroxetine or to any of the inactive ingredients in PAXIL CR [see Adverse Reactions (6.1, 6.2)].

5 WARNINGS AND PRECAUTIONS

5.1 Suicidal Thoughts and Behaviors in Adolescents and Young Adults

In pooled analyses of placebo-controlled trials of antidepressant drugs (SSRIs and other antidepressant classes) that included approximately 77,000 adult patients and 4,500 pediatric patients, the incidence of suicidal thoughts and behaviors in antidepressant-treated patients age 24 years and younger was greater than in placebo-treated patients. There was considerable variation in risk of suicidal thoughts and behaviors among drugs, but there was an increased risk identified in young patients for most drugs studied. There were differences in absolute risk of suicidal thoughts and behaviors across the different indications, with the highest incidence in patients with MDD. The drug-placebo differences in the number of cases of suicidal thoughts and behaviors per 1000 patients treated are provided in Table 2.

Table 2: Risk Differences of the Number of Patients of Suicidal Thoughts and Behaviors in the Pooled Placebo-Controlled Trials of Antidepressants in Pediatric and Adult Patients

Age Range | Drug-Placebo Difference in Number of Patients of Suicidal Thoughts and Behaviors per 1,000 Patients Treated
Increases Compared to Placebo
<18 years old | 14 additional patients
18-24 years old | 5 additional patients
Decreases Compared to Placebo
25-64 years old | 1 fewer patient
≥65 years old | 6 fewer patients

It is unknown whether the risk of suicidal thoughts and behaviors in children, adolescents, and young adults extends to longer-term use, i.e., beyond four months. However, there is substantial evidence from placebo-controlled maintenance trials in adults with MDD that antidepressants delay the recurrence of depression and that depression itself is a risk factor for suicidal thoughts and behaviors.

Monitor all antidepressant-treated patients for any indication for clinical worsening and emergence of suicidal thoughts and behaviors, especially during the initial few months of drug therapy, and at times of dosage changes. Counsel family members or caregivers of patients to monitor for changes in behavior and to alert the healthcare provider. Consider changing the therapeutic regimen, including possibly discontinuing PAXIL CR, in patients whose depression is persistently worse, or who are experiencing emergent suicidal thoughts or behaviors.

5.2 Serotonin Syndrome

Serotonin-norepinephrine reuptake inhibitors (SNRIs) and SSRIs, including PAXIL CR, can precipitate serotonin syndrome, a potentially life-threatening condition. The risk is increased with concomitant use of other serotonergic drugs (including triptans, tricyclic antidepressants, fentanyl, lithium, tramadol, meperidine, methadone, tryptophan, buspirone, amphetamines, and St. John's Wort) and with drugs that impair metabolism of serotonin, i.e., MAOIs [see Contraindications (4), Drug Interactions (7.1)]. Serotonin syndrome can also occur when these drugs are used alone.

Serotonin syndrome signs and symptoms may include mental status changes (e.g., agitation, hallucinations, delirium, and coma), autonomic instability (e.g., tachycardia, labile blood pressure, dizziness, diaphoresis, flushing, hyperthermia), neuromuscular symptoms (e.g., tremor, rigidity, myoclonus, hyperreflexia, incoordination), seizures, and gastrointestinal symptoms (e.g., nausea, vomiting, diarrhea).

The concomitant use of PAXIL CR with MAOIs is contraindicated. In addition, do not initiate PAXIL CR in a patient being treated with MAOIs such as linezolid or intravenous methylene blue. No reports involved the administration of methylene blue by other routes (such as oral tablets or local tissue injection). If it is necessary to initiate treatment with an MAOI such as linezolid or intravenous methylene blue in a patient taking PAXIL CR, discontinue PAXIL CR before initiating treatment with the MAOI [see Contraindications (4), Drug Interactions (7.1)].

Monitor all patients taking PAXIL CR for the emergence of serotonin syndrome. Discontinue treatment with PAXIL CR and any concomitant serotonergic agents immediately if the above symptoms occur, and initiate supportive symptomatic treatment. If concomitant use of PAXIL CR with other serotonergic drugs is clinically warranted, inform patients of the increased risk for serotonin syndrome and monitor for symptoms.

5.3 Drug Interactions Leading to QT Prolongation

The CYP2D6 inhibitory properties of paroxetine can elevate plasma levels of thioridazine and pimozide. Since thioridazine and pimozide given alone produce prolongation of the QTc interval and increase the risk of serious ventricular arrhythmias, the use of PAXIL CR is contraindicated in combination with thioridazine and pimozide [see Contraindications (4), Drug Interactions (7), Clinical Pharmacology (12.3)].

5.4 Embryofetal Toxicity

Based on meta-analyses of epidemiological studies, exposure to paroxetine in the first trimester of pregnancy is associated with a less than 2-fold increase in the rate of cardiovascular malformations among infants. For women who intend to become pregnant or who are in their first trimester of pregnancy, PAXIL CR, should be initiated only after consideration of the other available treatment options [see Use in Specific Populations (8.1)].

5.5 Increased Risk of Bleeding

Drugs that interfere with serotonin reuptake inhibition, including PAXIL CR, increase the risk of bleeding events. Concomitant use of aspirin, nonsteroidal anti-inflammatory drugs (NSAIDS), other antiplatelet drugs, warfarin, and other anticoagulants may add to this risk. Case reports and epidemiological studies (case‑control and cohort design) have demonstrated an association between use of drugs that interfere with serotonin reuptake and the occurrence of gastrointestinal bleeding. Based on data from the published observational studies, exposure to SSRIs, particularly in the month before delivery, has been associated with a less than 2-fold increase in the risk of postpartum hemorrhage [see Use in Specific Populations (8.1)]. Bleeding events related to drugs that interfere with serotonin reuptake have ranged from ecchymoses, hematomas, epistaxis, and petechiae to life-threatening hemorrhages.

Inform patients about the increased risk of bleeding associated with the concomitant use of PAXIL CR and antiplatelet agents or anticoagulants. For patients taking warfarin, carefully monitor the international normalized ratio.

5.6 Activation of Mania or Hypomania

In patients with bipolar disorder, treating a depressive episode with PAXIL CR or another antidepressant may precipitate a mixed/manic episode. During controlled clinical trials of immediate‑release paroxetine hydrochloride, hypomania or mania occurred in approximately 1% of paroxetine‑treated unipolar patients compared to 1.1% of active‑control and 0.3% of placebo‑treated unipolar patients. Prior to initiating treatment with PAXIL CR, screen patients for any personal or family history of bipolar disorder, mania, or hypomania.

5.7 Discontinuation Syndrome

Adverse reactions after discontinuation of serotonergic antidepressants, particularly after abrupt discontinuation, include: nausea, sweating, dysphoric mood, irritability, agitation, dizziness, sensory disturbances (e.g., paresthesia, such as electric shock sensations), tremor, anxiety, confusion, headache, lethargy, emotional lability, insomnia, hypomania, tinnitus, and seizures. A gradual reduction in dosage rather than abrupt cessation is recommended whenever possible [See Dosage and Administration (2.7)].

Adverse reactions have been reported upon discontinuation of treatment with paroxetine in pediatric patients. The safety and effectiveness of PAXIL CR in pediatric patients have not been established [see Boxed Warning, Warnings and Precautions (5.1), Use in Specific Populations (8.4)].

5.8 Seizures

PAXIL CR has not been systematically evaluated in patients with seizure disorders. Patients with history of seizures were excluded from clinical studies. PAXIL CR should be prescribed with caution in patients with a seizure disorder and should be discontinued in any patient who develops seizures.

5.9 Angle-Closure Glaucoma

The pupillary dilation that occurs following use of many antidepressant drugs including PAXIL CR may trigger an angle closure attack in a patient with anatomically narrow angles who does not have a patent iridectomy. Cases of angle-closure glaucoma associated with use of paroxetine hydrochloride tablets have been reported. Avoid use of antidepressants, including PAXIL CR, in patients with untreated anatomically narrow angles.

5.10 Hyponatremia

Hyponatremia may occur as a result of treatment with SNRIs and SSRIs, including PAXIL CR. Cases with serum sodium lower than 110 mmol/L have been reported. Signs and symptoms of hyponatremia include headache, difficulty concentrating, memory impairment, confusion, weakness, and unsteadiness, which may lead to falls. Signs and symptoms associated with more severe and/or acute cases have included hallucination, syncope, seizure, coma, respiratory arrest, and death. In many cases, this hyponatremia appears to be the result of the syndrome of inappropriate antidiuretic hormone secretion (SIADH).

In patients with symptomatic hyponatremia, discontinue PAXIL CR and institute appropriate medical intervention. Elderly patients, patients taking diuretics, and those who are volume-depleted may be at greater risk of developing hyponatremia with SNRIs and SSRIs. [see Use in Specific Populations (8.5)].

5.11 Reduction of Efficacy of Tamoxifen

Some studies have shown that the efficacy of tamoxifen, as measured by the risk of breast cancer relapse/mortality, may be reduced with concomitant use of paroxetine as a result of paroxetine’s irreversible inhibition of CYP2D6 and lower blood levels of tamoxifen [see Drug Interactions (7.1)]. One study suggests that the risk may increase with longer duration of coadministration. However, other studies have failed to demonstrate such a risk. When tamoxifen is used for the treatment or prevention of breast cancer, prescribers should consider using an alternative antidepressant with little or no CYP2D6 inhibition.

5.12 Bone Fracture

Epidemiological studies on bone fracture risk during exposure to some antidepressants, including SSRIs, have reported an association between antidepressant treatment and fractures. There are multiple possible causes for this observation, and it is unknown to what extent fracture risk is directly attributable to SSRI treatment.

5.13 Sexual Dysfunction

Use of SSRIs, including PAXIL CR, may cause symptoms of sexual dysfunction [see Adverse Reactions (6.1)]. In male patients, SSRI use may result in ejaculatory delay or failure, decreased libido, and erectile dysfunction. In female patients, SSRI use may result in decreased libido and delayed or absent orgasm.

It is important for prescribers to inquire about sexual function prior to initiation of PAXIL CR and to inquire specifically about changes in sexual function during treatment, because sexual function may not be spontaneously reported. When evaluating changes in sexual function, obtaining a detailed history (including timing of symptom onset) is important because sexual symptoms may have other causes, including the underlying psychiatric disorder. Discuss potential management strategies to support patients in making informed decisions about treatment.

6 ADVERSE REACTIONS

The following adverse reactions are included in more detail in other sections of the prescribing information:

- Hypersensitivity reactions to paroxetine [see Contraindications (4)]
- Suicidal Thoughts and Behaviors [see Warnings and Precautions (5.1)]
- Serotonin Syndrome [see Warnings and Precautions (5.2)]
- Embryofetal and Neonatal Toxicity [see Warnings and Precautions (5.4)]
- Increased Risk of Bleeding [see Warnings and Precautions (5.5)]
- Activation of Mania/Hypomania [see Warnings and Precautions (5.6)]
- Discontinuation Syndrome [see Warnings and Precautions (5.7)]
- Seizures [see Warnings and Precautions (5.8)]
- Angle-closure Glaucoma [see Warnings and Precautions (5.9)]
- Hyponatremia [see Warnings and Precautions (5.10)]
- Bone Fracture [see Warnings and Precautions (5.12)]
- Sexual Dysfunction [see Warnings and Precautions (5.13)]

6.1 Clinical Trials Experience

Because clinical trials are conducted under widely varying conditions, adverse reaction rates observed in the clinical trials of a drug cannot be directly compared to rates in the clinical trials of another drug and may not reflect the rates observed in practice.

Safety data for PAXIL CR is from 11 short-term, placebo‑controlled clinical trials including 3 studies in patients with major depressive disorder (MDD) (Studies 1, 2, and 3), 3 studies in patients with panic disorder (PD) (Studies 4, 5, and 6), 1 study in patients with social anxiety disorder (SAD) (Study 7), and 4 studies in female patients with premenstrual dysphoric disorder (PMDD) (Studies 8, 9, 10, and 11) [see Clinical Studies (14)]. These 11 trials included 1627 patients treated with Paxil CR.

- Studies 1 and 2 were 12-week studies that enrolled patients 18 to 65 years old who received PAXIL CR at doses ranging from 25 mg to 62.5 mg once daily. Study 3 was a 12-week study in patients 60 to 88 years old who received PAXIL CR at doses ranging from 12.5 mg to 50 mg once daily.
- Studies 4, 5, and 6 were 10-week studies in patients 19 to 72 years old who received PAXIL CR at doses ranging from 12.5 mg to 75 mg once daily.
- Study 7 was a 12-week study that enrolled adult patients who received PAXIL CR at doses ranging from 12.5 mg to 37.5 mg once daily.
- Studies 8, 9, and 10 were 12‑week, placebo‑controlled trials in female patients 18 to 46 years old who received PAXIL CR at doses of 12.5 mg or 25 mg once daily. Study 11 was a 12-week placebo‑controlled trial in patients 18 to 46 years old who received PAXIL CR 2 weeks prior to the onset of menses (luteal phase dosing) at doses of 12.5 mg or 25 mg once daily.

Adverse Reactions Leading to Discontinuation in Patients with MDD, PD, SAD, and PMDD

In pooled studies in patients with MDD, PD and SAD, the most common adverse reactions leading to study withdrawal were: nausea (up to 4% of patients), asthenia, headache, depression, insomnia, and abnormal liver function tests (each occurring in up to 2% of patients), and dizziness, somnolence, and diarrhea (each occurring in up to 1% of patients).

In pooled studies for PMDD, the most common adverse reactions leading to study withdrawal were: nausea (occurring in up to 6% of patients), asthenia (occurring in up to 5% of patients), somnolence (occurring in up to 4% of patients), insomnia (occurring in approximately 2% of patients); and impaired concentration, dry mouth, dizziness, decreased appetite, sweating, tremor, yawn and diarrhea (occurring in less than or equal to 2% of patients).

Adverse Reactions in MDD, PD, and SAD

Table 3 presents the most common adverse reactions in PAXIL CR-treated patients (incidence ≥5% and greater than placebo within at least 1 of the indications) in controlled trials in patients with MDD, PD, and SAD

Table 3. Adverse Reactions (³5% of Patients Treated with PAXIL CR and Greater than Placebo) in 10 to 12 Week Studies of MDD, PD, and SAD

 | MDD 18 to 65 year olds |  | MDD ≥60 years old |  | Panic Disorder |  | Social Anxiety Disorder
Body System/ Adverse Reaction | PAXIL CR (N=212) % | Placebo (N=211) % | PAXIL CR (N=104) % | Placebo (N=109) % | PAXIL CR (N=444) % | Placebo (N=445) % | PAXIL CR (N=186) % | Placebo (N=184) %
Body as a Whole
Headache | 27 | 20 | 17 | 13 | NA | NA | 23 | 17
Asthenia | 14 | 9 | 15 | 14 | 15 | 10 | 18 | 7
Abdominal Pain | 7 | 4 | - | - | 6 | 4 | 5 | 4
Back Pain | 5 | 3 | - | - | NA | NA | 4 | 1
Digestive System
Nausea | 22 | 10 | - | - | 23 | 17 | 22 | 6
Diarrhea | 18 | 7 | 15 | 9 | 12 | 9 | 9 | 8
Dry Mouth | 15 | 8 | 18 | 7 | 13 | 9 | 3 | 2
Constipation | 10 | 4 | 13 | 5 | 9 | 6 | 5 | 2
Flatulence | 6 | 4 | - | - | NA | NA | NA | NA
Decreased Appetite |  | 2 | 12 | 5 | 8 | 6 | 1 | <1
Dyspepsia | NA | NA | 13 | 10 | NA | NA | 2 | <1
Musculoskeletal System
Myalgia | NA | NA | - | - | 5 | 3 | NA | NA
Nervous System
Somnolence | 22 | 8 | 21 | 12 | 20 | 9 | 9 | 4
Insomnia | 17 | 9 | 10 | 8 | 20 | 11 | 9 | 4
Dizziness | 14 | 4 | 9 | 5 | NA | NA | 7 | 4
Libido Decreased | 7 | 3 | 8 | <1 | 9 | 4 |  | 1
Nervousness | NA | NA | - | - | 8 | 7 | NA | NA
Tremor | 7 | 1 | 7 | 0 | 8 | 2 | 4 | 2
Anxiety | NA | NA | - | - | 5 | 4 | 2 | 1
Respiratory System
Sinusitis | NA | NA | - | - | 8 | 5 | NA | NA
Yawn |  | 0 | - | - | 3 | 0 | 2 | 0
Skin and Appendages
Sweating | 6 | 2 | 10 | <1 | 7 | 2 | 14 | 3
Special Senses
Abnormal Visiona | 5 | 1 | - | - | 3 | <1 | 2 | 0
Urogenital System
Abnormal Ejaculationb,c | 26 | 1 | 17 | 3 | 27 | 3 | 15 | 1
Female Genital Disorderb,d | 10 | <1 | - | - | 7 | 1 | 3 | 0
Impotenceb | 5 | 3 | 9 | 3 | 10 | 1 | 9 | 0

Hyphen = the reaction listed occurred in <5% of patients treated with PAXIL CR

NA = the adverse reaction listed did not occur in this group of patients

a Mostly blurred vision

b Based on the number of males or females

c Mostly anorgasmia or delayed ejaculation

d Mostly anorgasmia or delayed orgasm

Other Adverse Reactions Observed During the Premarketing Evaluation of PAXIL CR

Adverse reactions from studies in MDD (not including Study 3 in elderly patients), PD, and SAD that occurred between 1% and 5% of patients treated with PAXIL CR and at a rate greater than in placebo-treated patients include:, allergic reaction, tachycardia, vasodilatation, hypertension, migraine, vomiting, weight loss, weight gain, hypertonia, paresthesia, agitation, confusion, myoclonus, concentration impaired, depression, rhinitis, cough increased, bronchitis, photosensitivity, eczema, taste perversion, UTI, menstrual disorder, urinary frequency, urination impaired, and vaginitis.

Adverse Reactions in Patients with PMDD

Table 4 displays adverse reactions that occurred (incidence of 5% or more and greater than placebo within at least 1 of the studies) in patients treated with PAXIL CR in Studies 8, 9, 10, and 11.

Table 4. Adverse Reactions (≥5% of Patients Treated with PAXIL CR and Greater than Placebo) in Pooled Studies PMDD (Studies 8, 9, 11), and in Study 10a,b,c

Body System/ Adverse Reaction | % Reporting Adverse Reaction
Body System/ Adverse Reaction | Continuous Dosing |  | Luteal Phase Dosing
Body System/ Adverse Reaction | PAXIL CR (n = 681) % | Placebo (n = 349)% | PAXIL CR (n = 246)% | Placebo (n = 120)%%
Body as a Whole
Asthenia | 17 | 6 | 15 | 4
Headache | 15 | 12 | NA | NA
Infection | 6 | 4 | NA | NA
Digestive System
Nausea | 17 | 7 | 18 | 2
Diarrhea | 6 | 2 | 6 | 0
Constipation | 5 | 1 | 2 | <1
Nervous System
Libido Decreased | 12 | 5 | 9 | 6
Somnolence | 9 | 2 | 3 | <1
Insomnia | 8 | 2 | 7 | 3
Dizziness | 7 | 3 | 6 | 3
Tremor | 4 | <1 | 5 | 0
Skin and Appendages
Sweating | 7 | <1 | 6 | <1
Urogenital System
Female Genital Disordersc | 8 | 1 | 2 | 0

NA= the adverse reaction information is not available in this population.

a <1% means greater than zero and less than 1%.

b The luteal phase and continuous dosing PMDD trials were not designed for making direct comparisons between the 2 dosing regimens.

c Mostly anorgasmia or difficulty achieving orgasm.

Dose Dependent Adverse Reactions

Comparison of the incidence of adverse reactions (placebo vs. 12.5 mg PAXIL CR vs. 25 mg PAXIL CR) from studies 8, 9, 10 showed the following adverse reactions to be dose-related: Nausea, somnolence, sweating, dry mouth, dizziness, decreased appetite, tremor, impaired concentration, yawn, paresthesia, hyperkinesia, and vaginitis.

Male and Female Sexual Dysfunction

Although changes in sexual desire, sexual performance, and sexual satisfaction often occur as manifestations of a psychiatric disorder, they may also be a consequence of SSRI treatment. However, reliable estimates of the incidence and severity of untoward experiences involving sexual desire, performance, and satisfaction are difficult to obtain, in part because patients and healthcare providers may be reluctant to discuss them. Accordingly, estimates of the incidence of untoward sexual experience and performance cited in labeling may underestimate their actual incidence.

The percentage of patients reporting symptoms of sexual dysfunction in the Studies 1 and 2 (nonelderly patients with MDD), 4, 5, 6, 7, 8, 9, 10, and 11 are presented in Table 5:

Table 5. Adverse Reactions Related To Sexual Dysfunction In Patients Treated With PAXIL CR in Pooled 10-12 Week Studies of MDD, PD, SAD, and PMDD

 | Studies 1 and 2 % |  | Studies 4, 5 and 6 % |  | Study 7 % |  | Studies 8, 9 and 11 (Continuous Dosing) % |  | Study 10 (Luteal Phase Dosing) %
 | PAXIL CR | Placebo | PAXIL CR | Placebo | PAXIL CR | Placebo | PAXIL CR | Placebo | PAXIL CR | Placebo
n (males) | 78 | 78 | 162 | 194 | 88 | 97 | NA | NA | NA | NA
Decreased Libido | 10 | 5 | 9 | 6 | 13 | 1 | NA | NA | NA | NA
Abnormal ejaculation | 26 | 1 | 27 | 3 | 15 | 1 | NA | NA | NA | NA
Impotence | 5 | 3 | 10 | 1 | 9 | 0 | NA | NA | NA | NA
n (females) | 134 | 133 | 282 | 251 | 98 | 87 | 681 | 349 | 246 | 120
Decreased Libido | 4 | 2 | 8 | 2 | 4 | 1 | 12 | 5 | 9 | 6
Orgasmic Disturbance | 10 | <1 | 7 | 1 | 3 | 0 | 8 | 1 | 2 | 0

NA = the adverse reaction listed did not occur in this group of patients.

Paroxetine treatment has been associated with several cases of priapism. In those cases with a known outcome, patients recovered without sequelae.

Less Common Adverse Reactions

The following adverse reactions occurred during the clinical studies of PAXIL CR and are not included elsewhere in the labeling.

Reactions are categorized by body system and listed in order of decreasing frequency according to the following definitions: Frequent adverse reactions are those occurring on 1 or more occasions in at least 1/100 patients; infrequent adverse reactions are those occurring in 1/100 to 1/1,000 patients; rare reactions are those occurring in fewer than 1/1,000 patients.

Cardiovascular System: Infrequent was postural hypotension.

Hemic and Lymphatic System: Rare was thrombocytopenia.

Metabolic and Nutritional Disorders: Infrequent were generalized edema and hypercholesteremia.

Nervous System: Infrequent were convulsion, akathisia, and manic reaction.

Psychiatric: Infrequent were hallucinations.

Skin and Appendages: Frequent was rash; infrequent was urticaria; rare was angioedema and erythema multiforme.

Urogenital System: Infrequent was urinary retention; rare was urinary incontinence.

6.2 Postmarketing Experience

The following reactions have been identified during post approval use of paroxetine. Because these reactions are reported voluntarily from a population of unknown size, it is not always possible to reliably estimate their frequency or establish a causal relationship to drug exposure.

Acute pancreatitis, elevated liver function tests (the most severe cases were deaths due to liver necrosis, and grossly elevated transaminases associated with severe liver dysfunction), Guillain‑Barré syndrome, Stevens-Johnson syndrome, toxic epidermal necrolysis, drug reaction with eosinophilia and systemic symptoms (DRESS), priapism, syndrome of inappropriate ADH secretion (SIADH), prolactinemia and galactorrhea; extrapyramidal symptoms which have included akathisia, bradykinesia, cogwheel rigidity, dystonia, hypertonia, trismus; status epilepticus, acute renal failure, pulmonary hypertension, allergic alveolitis, anosmia, hyposmia, anaphylaxis, eclampsia, laryngismus, optic neuritis, porphyria, restless legs syndrome (RLS), ventricular fibrillation, ventricular tachycardia (including torsade de pointes), hemolytic anemia, events related to impaired hematopoiesis (including aplastic anemia, pancytopenia, bone marrow aplasia, and agranulocytosis), and vasculitic syndromes (such as Henoch‑Schönlein purpura).

7 DRUG INTERACTIONS

7.1 Clinically Significant Drug Interactions

Table 6 includes clinically significant drug interactions with PAXIL CR.

Table 6: Clinically Significant Drug Interactions with PAXIL CR

Monoamine Oxidase Inhibitors (MAOIs)
Clinical Impact | The concomitant use of SSRIs, including PAXIL CR, and MAOIs increases the risk of serotonin syndrome.
Intervention | PAXIL CR is contraindicated in patients taking MAOIs, including MAOIs such as linezolid or intravenous methylene blue [see Dosage and Administration (2.6), Contraindications (4), Warnings and Precautions (5.2)].
Examples | selegiline, tranylcypromine, isocarboxazid, phenelzine, linezolid, methylene blue
Pimozide and Thioridazine
Clinical Impact | Increased plasma concentrations of pimozide and thioridazine, drugs with a narrow therapeutic index, may increase the risk of QTc prolongation and ventricular arrhythmias.
Intervention | PAXIL CR is contraindicated in patients taking pimozide or thioridazine [see Contraindications (4)].
Other Serotonergic Drugs
Clinical Impact | The concomitant use of serotonergic drugs with PAXIL CR increases the risk of serotonin syndrome.
Intervention | Monitor patients for signs and symptoms of serotonin syndrome, particularly during treatment initiation and dosage increases. If serotonin syndrome occurs, consider discontinuation of PAXIL CR and/or concomitant serotonergic drugs [see Warnings and Precautions (5.2)].
Examples | Other SSRIs, SNRIs, triptans, tricyclic antidepressants, opioids, lithium, tryptophan, buspirone, St. John’s Wort
Drugs that Interfere with Hemostasis (antiplatelet agents and anticoagulants)
Clinical Impact | The concurrent use of an antiplatelet agent or anticoagulant with PAXIL CR may potentiate the risk of bleeding.
Intervention | Inform patients of the increased risk of bleeding associated with the concomitant use of PAXIL CR and antiplatelet agents and anticoagulants. For patients taking warfarin, carefully monitor the international normalized ratio [see Warnings and Precautions (5.5)].
Examples | aspirin, clopidogrel, heparin, warfarin
Drugs Highly Bound to Plasma Protein
Clinical Impact | PAXIL CR is highly bound to plasma protein. The concomitant use of PAXIL CR with another drug that is highly bound to plasma protein may increase free concentrations of PAXIL CR or other tightly-bound drugs in plasma.
Intervention | Monitor for adverse reactions and reduce dosage of PAXIL CR or other protein-bound drugs as warranted.
Examples | warfarin
Drugs Metabolized by CYP2D6
Clinical Impact | PAXIL CR is a CYP2D6 inhibitor [see Clinical Pharmacology (12.3)]. The concomitant use of PAXIL CR with a CYP2D6 substrate may increase the exposure of the CYP2D6 substrate.
Intervention | Decrease the dosage of a CYP2D6 substrate if needed with concomitant PAXIL CR use. Conversely, an increase in dosage of a CYP2D6 substrate may be needed if PAXIL CR is discontinued.
Examples | propafenone, flecainide, atomoxetine, desipramine, dextromethorphan, metoprolol, nebivolol, perphenazine, tolterodine, venlafaxine, risperidone.
Tamoxifen
Clinical Impact | Concomitant use of tamoxifen with PAXIL CR may lead to reduced plasma concentrations of the active metabolite (endoxifen) and reduced efficacy of tamoxifen
Intervention | Consider use of an alternative antidepressant little or no CYP2D6 inhibition [see Warnings and Precautions (5.11)].
Fosamprenavir/Ritonavir
Clinical Impact | Co-administration of fosamprenavir/ritonavir with paroxetine significantly decreased plasma levels of paroxetine.
Intervention | Any dose adjustment should be guided by clinical effect (tolerability and efficacy).

8 USE IN SPECIFIC POPULATIONS

8.1 Pregnancy

Pregnancy Exposure Registry

There is a pregnancy exposure registry that monitors pregnancy outcomes in women exposed to antidepressants during pregnancy. Healthcare providers are encouraged to register patients by calling the National Pregnancy Registry for Antidepressants at 1-866-961-2388 or visiting online at https://womensmentalhealth.org/clinical-and-researchprograms/ pregnancyregistry/antidepressants/.

Risk Summary

Based on data from published observational studies, exposure to SSRIs, particularly in the month before delivery, has been associated with a less than 2-fold increase in the risk of postpartum hemorrhage [see Warnings and Precautions (5.5) and Clinical Considerations].

PAXIL CR is associated with a less than 2-fold increase in cardiovascular malformations when administered to a pregnant woman during the first trimester. While individual epidemiological studies on the association between paroxetine use and cardiovascular malformations have reported inconsistent findings, some meta-analyses of epidemiological studies have identified an increased risk of cardiovascular malformations (see Data). There are risks of persistent pulmonary hypertension of the newborn (PPHN) (see Data) and/or poor neonatal adaptation with exposure to selective serotonin reuptake inhibitors (SSRIs), including PAXIL CR, during pregnancy. There also are risks associated with untreated depression in pregnancy (see Clinical Considerations). For women who intend to become pregnant or who are in their first trimester of pregnancy, paroxetine should be initiated only after consideration of the other available treatment options.

No evidence of treatment related malformations was observed in animal reproduction studies, when paroxetine was administered during the period of organogenesis at doses up to 50 mg/kg/day in rats and 6 mg/kg/day in rabbits. These doses are approximately 6 (rat) and less than 2 (rabbit) times the maximum recommended human dose (MRHD – 75 mg) on an mg/m^2 basis. When paroxetine was administered to female rats during the last trimester of gestation and continued through lactation, there was an increase in the number of pup deaths during the first four days of lactation. This effect occurred at a dose of 1 mg/kg/day which is less than the MRHD on an mg/m^2 basis (see Data).

The estimated background risks of major birth defects and miscarriage for the indicated populations are unknown. All pregnancies have a background risk of birth defect, loss, or other adverse outcomes. In the US general population, the estimated background risk of major birth defects and miscarriage in clinically recognized pregnancies is 2 to 4% and 15 to 20%, respectively.

Clinical Considerations

Disease-associated maternal and/or embryo/fetal risk

Women who discontinue antidepressants during pregnancy are more likely to experience a relapse of major depression than women who continue antidepressants. This finding is from a prospective longitudinal study of 201 pregnant women with a history of major depressive disorder who were euthymic and taking antidepressants at the beginning of pregnancy. Consider the risks of untreated depression when discontinuing or changing treatment with antidepressant medication during pregnancy and postpartum.

Maternal Adverse Reactions

Use of PAXIL CR in the month before delivery may be associated with an increased risk of postpartum hemorrhage [see Warnings and Precautions (5.5)].

Fetal/Neonatal adverse reactions Neonates exposed to PAXIL CR and other SSRIs late in the third trimester have developed complications requiring prolonged hospitalization, respiratory support, and tube feeding. Such complications can arise immediately upon delivery. Reported clinical findings have included respiratory distress, cyanosis, apnea, seizures, temperature instability, feeding difficulty, vomiting, hypoglycemia, hypotonia, hypertonia, hyperreflexia, tremors, jitteriness, irritability, and constant crying. These findings are consistent with either a direct toxic effect of SSRIs or possibly a drug discontinuation syndrome. It should be noted that, in some cases, the clinical picture is consistent with serotonin syndrome [see Warnings and Precautions (5.4)].

Data

Human Data

Published epidemiological studies on the association between first trimester paroxetine use and cardiovascular malformations have reported inconsistent results; however, meta-analyses of population-based cohort studies published between 1996-2017 indicate a less than 2-fold increased risk for overall cardiovascular malformations. Specific cardiac malformations identified in two meta-analyses include approximately 2 to 2.5-fold increased risk for right ventricular outflow tract defects. One meta-analysis also identified an increased risk (less than 2- fold) for bulbus cordis anomalies and anomalies of cardiac septal closure, and an increased risk for atrial septal defects (pooled OR 2.38, 95% CI 1.14-4.97). Important limitations of the studies included in these meta-analyses include potential confounding by indication, depression severity, and potential exposure misclassification.

Exposure to SSRIs, particularly later in pregnancy, may have an increased risk for PPHN. PPHNoccurs in 1-2 per 1000 live births in the general population and is associated with substantialneonatal morbidity and mortality.

Animal Data

Reproduction studies were performed at doses up to 50 mg/kg/day in rats and 6 mg/kg/day in rabbits administered during organogenesis. These doses are approximately 6 (rat) and less than 2 (rabbit) times the maximum recommended human dose (MRHD – 75 mg) on an mg/m^2 basis. These studies have revealed no evidence of malformations. However, in rats, there was an increase in pup deaths during the first 4 days of lactation when dosing occurred during the last trimester of gestation and continued throughout lactation. This effect occurred at a dose of 1 mg/kg/day which is less than the MRHD on an mg/m^2 basis. The no‑effect dose for rat pup mortality was not determined. The cause of these deaths is not known.

8.2 Lactation

Risk Summary

Data from the published literature report the presence of paroxetine in human milk (see Data).There are reports of agitation, irritability, poor feeding and poor weight gain in infants exposedto paroxetine through breast milk (see Clinical Considerations). There are no data on the effectsof paroxetine on milk production. The developmental and health benefits of breastfeeding shouldbe considered along with the mother's clinical need for PAXIL CR and any potential adverse effects on the breastfed infant from PAXIL CR or the underlying maternal condition.

Clinical Considerations

Infants exposed to PAXIL CR should be monitored for agitation, irritability, poor feeding andpoor weight gain.

Data

Published literature suggests the presence of paroxetine in human milk with relative infant dosesranging between 0.4% to 2.2%, and a milk: plasma ratio of <1. No significant amounts weredetected in the plasma of infants after breastfeeding.

8.3 Females and Males of Reproductive Potential

Infertility

Male

Based on findings from clinical studies, paroxetine may affect sperm quality which may impairfertility; it is not known if this effect is reversible [see Nonclinical Toxicology (13.1)].

8.4 Pediatric Use

The safety and effectiveness of PAXIL CR in pediatric patients have not been established [see Boxed Warning, Warnings and Precautions (5.1)].

Three placebo-controlled trials in 752 pediatric patients with MDD have been conducted with immediate-release paroxetine, and effectiveness was not established in pediatric patients. Decreased appetite and weight loss have been observed in association with the use of SSRIs.

In placebo-controlled clinical trials conducted with pediatric patients, the following adverse reactions were reported in at least 2% of pediatric patients treated with immediate-release paroxetine hydrochloride and at a rate at least twice that for pediatric patients receiving placebo: emotional lability (including self-harm, suicidal thoughts, attempted suicide, crying, and mood fluctuations), hostility, decreased appetite, tremor, sweating, hyperkinesia, and agitation.

Adverse reactions upon discontinuation of treatment with immediate-release paroxetine hydrochloride in the pediatric clinical trials that included a taper phase regimen, which occurred in at least 2% of patients and at a rate at least twice that of placebo, were: emotional lability (including suicidal ideation, suicide attempt, mood changes, and tearfulness), nervousness, dizziness, nausea, and abdominal pain.

8.5 Geriatric Use

SSRIs and SNRIs, including PAXIL CR, have been associated with cases of clinically significant hyponatremia in elderly patients, who may be at greater risk for this adverse reaction [see Warnings and Precautions (5.9)].

In premarketing clinical trials with immediate‑release paroxetine hydrochloride, 17% of paroxetine treated patients (approximately 700) were 65 years or older. Pharmacokinetic studies revealed a decreased clearance in the elderly, and a lower starting dose is recommended; however, no overall differences in safety or effectiveness were observed between these subjects and younger subjects [see Dosage and Administration (2.5) and Clinical Pharmacology (12.3)].

8.6 Renal and/or Hepatic Impairment

Increased plasma concentrations of paroxetine occur in patients with renal and hepatic impairment. The initial dosage of PAXIL CR should be reduced in patients with severe renal impairment and patients with severe hepatic impairment [see Dosage and Administration (2.5) and Clinical Pharmacology (12.3)].

10 OVERDOSAGE

The following have been reported with paroxetine tablet overdosage:

- Seizures, which may be delayed, and altered mental status including coma.
- Cardiovascular toxicity, which may be delayed, including QRS and QTc interval prolongation. Hypertension most commonly seen, but rarely can see hypotension alone or with co-ingestants including alcohol.
- Serotonin syndrome (patients with a multiple drug overdosage with other proserotonergic drugs may have a higher risk).

Gastrointestinal decontamination with activated charcoal should be considered in patients who present early after a paroxetine overdose.

Consider contacting a Poison Center (1-800-222-1222) or a medical toxicologist for additional overdosage management recommendations.

11 DESCRIPTION

PAXIL CR, contains paroxetine hydrochloride, an SSRI. It is the hydrochloride salt of a phenylpiperidine compound identified chemically as (-)-trans-4R-(4'-fluorophenyl)-3S-[(3',4'-methylenedioxyphenoxy) methyl] piperidine hydrochloride hemihydrate and has the empirical formula of C19H20FNO3·HCl·1/2H2O. The molecular weight is 374.8 g/mol (329.4 g/mol as free base). The structural formula of paroxetine hydrochloride is:

Paroxetine hydrochloride is an odorless, off‑white powder, having a melting point range of 120° C to 138°C and a solubility of 5.4 mg/mL in water.

PAXIL CR tablets are intended for oral administration. Each extended‑release tablet contains 12.5 mg, 25 mg, or 37.5 mg paroxetine equivalent to 14.25 mg, 28.51 mg, or 42.76 mg of paroxetine hydrochloride, respectively. One layer of the tablet consists of a degradable barrier layer and the other contains the active material in a hydrophilic matrix.

Inactive ingredients consist of glyceryl behenate, hypromellose, lactose monohydrate, magnesium stearate, methacrylic acid copolymer type C, polyethylene glycols, polysorbate 80, polyvinylpyrrolidone, silicon dioxide, sodium lauryl sulfate, talc, titanium dioxide, triethyl citrate and the following colorants: D&C Red No. 30 aluminum lake (25 mg), D&C Yellow No. 10 aluminum lake (12.5 mg), FD&C Blue No. 2 aluminum lake (37.5 mg), FD&C Yellow No. 6 aluminum lake (12.5 mg), red ferric oxide (25 mg) and Yellow ferric oxide (12.5 mg and 37.5 mg).

12 CLINICAL PHARMACOLOGY

12.1 Mechanism of Action

The mechanism of action of paroxetine in the treatment of major depressive disorder (MDD), panic disorder (PD), social anxiety disorder (SAD), and premenstrual dysphoric disorder (PMDD) is unknown, but is presumed to be linked to potentiation of serotonergic activity in the central nervous system resulting from inhibition of neuronal reuptake of serotonin (5-HT).

12.2 Pharmacodynamics

Studies at clinically relevant doses in humans have demonstrated that paroxetine blocks the uptake of serotonin into human platelets. In vitro studies in animals also suggest that paroxetine is a potent and highly selective inhibitor of neuronal serotonin reuptake (SSRI) and has only very weak effects on norepinephrine and dopamine neuronal reuptake.

12.3 Pharmacokinetics

Absorption

Tablets of PAXIL CR contain a degradable polymeric matrix designed to control the dissolution rate of paroxetine over a period of approximately 4 to 5 hours. In addition to controlling the rate of drug release in vivo, an enteric coat delays the start of drug release until tablets of PAXIL CR have left the stomach.

Paroxetine extended-release tablets are completely absorbed after oral dosing of a solution of the hydrochloride salt. In a study in which normal male and female subjects (n = 23) received single oral doses of PAXIL CR at 4 dosage strengths (12.5 mg, 25 mg, 37.5 mg, and 50 mg), paroxetine Cmax and AUC0-inf increased disproportionately with dose (as seen also with immediate‑release formulations). Mean Cmax and AUC0-inf values at these doses were 2.0, 5.5, 9.0, and 12.5 ng/mL, and 121, 261, 338, and 540 ng·hr. /mL, respectively. Tmax was observed typically between 6 and 10 hours post‑dose, reflecting a reduction in absorption rate compared with immediate‑release formulations. The bioavailability of 25 mg PAXIL CR is not affected by food.

Distribution

Paroxetine distributes throughout the body, including the CNS, with only 1% remaining in the plasma.

Approximately 95% and 93% of paroxetine is bound to plasma protein at 100 ng/mL and 400 ng/mL, respectively. Under clinical conditions, paroxetine concentrations would normally be less than 400 ng/mL. Paroxetine does not alter the in vitro protein binding of phenytoin or warfarin.

Elimination

Metabolism

The mean elimination half-life of paroxetine was 15 to 20 hours throughout a range of single doses of PAXIL CR (12.5 mg, 25 mg, 37.5 mg, and 50 mg). During repeated administration of PAXIL CR (25 mg once daily), steady state was reached within 2 weeks (i.e., comparable to immediate‑release formulations). In a repeat‑dose study in which normal male and female subjects (n = 23) received PAXIL CR (25 mg daily), mean steady state Cmax, Cmin, and AUC0-24 values were 30 ng/mL, 20 ng/mL, and 550 ng·hr./mL, respectively.

Based on studies using immediate‑release formulations, steady‑state drug exposure based on AUC0-24 was several‑fold greater than would have been predicted from single‑dose data. The excess accumulation is a consequence of the fact that 1 of the enzymes that metabolizes paroxetine is readily saturable.

In steady‑state dose proportionality studies involving elderly and nonelderly patients, at doses of the immediate‑release formulation of 20 mg to 40 mg daily for the elderly and 20 mg to 50 mg daily for the nonelderly, some nonlinearity was observed in both populations, again reflecting a saturable metabolic pathway (Figure 3).

Paroxetine is extensively metabolized after oral administration. The principal metabolites are polar and conjugated products of oxidation and methylation, which are readily cleared. Conjugates with glucuronic acid and sulfate predominate, and major metabolites have been isolated and identified. Data indicate that the metabolites have no more than 1/50 the potency of the parent compound at inhibiting serotonin uptake. The metabolism of paroxetine is accomplished in part by CYP2D6. Saturation of this enzyme at clinical doses appears to account for the nonlinearity of paroxetine kinetics with increasing dose and increasing duration of treatment. The role of this enzyme in paroxetine metabolism also suggests potential drug‑drug interactions [see Drug Interactions (7.3)].

Excretion

Approximately 64% of a 30‑mg oral solution dose of paroxetine was excreted in the urine with 2% as the parent compound and 62% as metabolites over a 10‑day post‑dosing period. About 36% was excreted in the feces (probably via the bile), mostly as metabolites and less than 1% as the parent compound over the 10‑day post‑dosing period.

The elimination half-life is approximately 15 to 20 hours after a single dose of PAXIL CR. Paroxetine metabolism is mediated in part by CYP2D6, and the metabolites are primarily excreted in the urine and to some extent in the feces. Pharmacokinetic behavior of paroxetine has not been evaluated in subjects who are deficient in CYP2D6 (poor metabolizers).

Drug Interaction Studies

There are clinically significant, known drug interactions between paroxetine and other drugs [see Drug Interactions (7)].

Figure 1. Impact of Paroxetine on the Pharmacokinetics of Co-Administered Drugs (log scale)

Figure 2. Impact of Co-Administered Drugs on the Pharmacokinetics of Paroxetine

Theophylline: Reports of elevated theophylline levels associated with immediate‑release paroxetine treatment have been reported. While this interaction has not been formally studied, it is recommended that theophylline levels be monitored when these drugs are concurrently administered.

Drugs Metabolized by Cytochrome CYP3A4

An in vivo interaction study involving the coadministration under steady‑state conditions of paroxetine and terfenadine, a substrate for CYP3A4, revealed no effect of paroxetine on terfenadine pharmacokinetics. In addition, in vitro studies have shown ketoconazole, a potent inhibitor of CYP3A4 activity, to be at least 100 times more potent than paroxetine as an inhibitor of the metabolism of several substrates for this enzyme, including terfenadine, astemizole, cisapride, triazolam, and cyclosporine. Paroxetine’s extent of inhibition of CYP3A4 activity is not expected to be of clinical significance.

Specific Populations

The impact of specific populations on the pharmacokinetics of paroxetine are shown in Figure 3

13 NONCLINICAL TOXICOLOGY

13.1 Carcinogenesis, Mutagenesis, Impairment of Fertility

Carcinogenesis

Two‑year carcinogenicity studies were conducted in rodents given paroxetine in the diet at 1, 5, and 25 mg/kg/day (mice) and 1, 5, and 20 mg/kg/day (rats). These doses are up to approximately 1.6 (mouse) and 2.5 (rat) times the MRHD on an mg/m^2 basis. There was a significantly greater number of male rats in the high‑dose group with reticulum cell sarcomas (1/100, 0/50, 0/50, and 4/50 for control, low‑, middle‑, and high‑dose groups, respectively) and a significantly increased linear trend across dose groups for the occurrence of lymphoreticular tumors in male rats. Female rats were not affected. Although there was a dose‑related increase in the number of tumors in mice, there was no drug‑related increase in the number of mice with tumors. The relevance of these findings to humans is unknown.

Mutagenesis

Paroxetine produced no genotoxic effects in a battery of 5 in vitro and 2 in vivo assays that included the following: Bacterial mutation assay, mouse lymphoma mutation assay, unscheduled DNA synthesis assay, and tests for cytogenetic aberrations in vivo in mouse bone marrow and in vitro in human lymphocytes and in a dominant lethal test in rats.

Impairment of Fertility

A reduced pregnancy rate was found in reproduction studies in rats at a dose of paroxetine of 15 mg/kg/day, which is approximately twice the MRHD on an mg/m^2 basis. Irreversible lesions occurred in the reproductive tract of male rats after dosing in toxicity studies for 2 to 52 weeks. These lesions consisted of vacuolation of epididymal tubular epithelium at 50 mg/kg/day and atrophic changes in the seminiferous tubules of the testes with arrested spermatogenesis at 25 mg/kg/day (approximately 6 and 3 times the MRHD on an mg/m^2 basis).

14 CLINICAL STUDIES

14.1 Major Depressive Disorder

The efficacy of PAXIL CR as a treatment for major depressive disorder (MDD) was established in two 12‑week, multicenter, randomized, double-blind, placebo‑controlled, flexible dose studies with PAXIL CR (Study 1 and Study 2) in adult patients who met Diagnostic and Statistical Manual of Mental Disorders (DSM)‑IV criteria for MDD. Study 1 and 2 included patients 18 to 65 years old who received PAXIL CR doses of 25 to 62.5 mg/day (N= 212) or placebo (N= 211) once daily compared to immediate-release paroxetine 20 to 50 mg (N=217). A third 12-week, multicenter, randomized, double-blind, placebo‑controlled, flexible dose study with PAXIL CR (Study 3) included elderly patients, ranging in age from 60 to 88 years old and used PAXIL CR doses of 12.5 to 50 mg/day (N=104) or placebo (N=109) once daily compared to immediate-release paroxetine 10 to 40 mg (N=106). In all three studies, PAXIL CR was statistically superior to placebo in improving depressive symptoms as measured by the following: the mean change from baseline in the Hamilton Depression Rating Scale (HDRS) total score at Week 12, the mean change from baseline in the Hamilton Depressed Mood item score at Week 12, and the mean change from baseline in the Clinical Global Impression (CGI)–Severity of Illness score.

Long-term efficacy of paroxetine for treatment of MDD in outpatients was established with one randomized withdrawal study with immediate-release paroxetine. Patients who responded to immediate‑release paroxetine (HDRS total score <8) during an initial 8‑week open‑label treatment phase were then randomized to continue immediate‑release paroxetine or placebo, for up to 1 year. Patients treated with immediate‑release paroxetine demonstrated a statistically significant lower relapse rate during the withdrawal phase (15%) compared to those on placebo (39%). Effectiveness was similar for male and female patients.

14.2 Panic Disorder

The effectiveness of PAXIL CR in the treatment of panic disorder (PD) was evaluated in three 10‑week, multicenter, flexible‑dose studies (Studies 4, 5, and 6) comparing PAXIL CR (12.5 to 75 mg daily) to placebo in adult outpatients 19 to 72 years of age who met panic disorder (with or without agoraphobia) criteria according to DSM‑IV. These trials were assessed on the basis of their outcomes on 3 variables: (1) the proportions of patients free of full panic attacks at Week 10; (2) change from baseline to Week 10 in the median number of full panic attacks; and (3) change from baseline to Week 10 in the median Clinical Global Impression Severity score. For Studies 4 and 5, PAXIL CR was superior to placebo on 2 of these 3 variables. Study 6 failed to consistently demonstrate a statistically significant difference between PAXIL CR and placebo on any of these variables.

For all 3 studies, the mean dose of PAXIL CR for completers at Week 10 was approximately 50 mg/day. Subgroup analyses did not indicate that there were any differences in treatment outcomes as a function of age or gender.

Long‑term maintenance effects of paroxetine in patients with PD were demonstrated in a randomized-withdrawal study using immediate‑release paroxetine. Patients who were responders during a 10‑week, double‑blind trial (followed by a 3-month double-blind maintenance phase) of immediate‑release paroxetine were re-randomized to continue immediate‑release paroxetine or placebo in a 3‑month, double‑blind withdrawal phase. Patients randomized to immediate-release paroxetine were statistically significantly less likely to relapse than placebo-treated patients.

14.3 Social Anxiety Disorder

The efficacy of PAXIL CR as a treatment for social anxiety disorder (SAD) was established, in part, on the basis of extrapolation from the established effectiveness of immediate‑release paroxetine in the treatment of SAD. In addition, the effectiveness of PAXIL CR in the treatment of SAD was demonstrated in one 12‑week, multicenter, double‑blind, flexible‑dose, placebo‑controlled study of adult outpatients with a primary diagnosis of SAD by DSM‑IV criteria (Study 7). In Study 7, the effectiveness of PAXIL CR (12.5 to 37.5 mg daily) compared to placebo was evaluated on the basis of (1) change from baseline in the Liebowitz Social Anxiety Scale (LSAS) total score at Week 12 and (2) the proportion of responders who scored 1 or 2 (very much improved or much improved) on the CGI Global Improvement score at Week 12.

In Study 7, PAXIL CR demonstrated statistically significant superiority over placebo on both the change on LSAS total score at Week 12 and the CGI Improvement responder criterion at Week 12. For patients who completed the trial, 64% of patients treated with PAXIL CR compared to 35% of patients treated with placebo were CGI Improvement responders at Week 12.

Subgroup analyses did not indicate that there were any differences in treatment outcomes as a function of gender. Subgroup analyses of studies utilizing the immediate‑release formulation of paroxetine generally did not indicate differences in treatment outcomes as a function of age, race, or gender.

14.4 Premenstrual Dysphoric Disorder

The effectiveness of PAXIL CR for the treatment of Premenstrual Dysphoric Disorder (PMDD) utilizing a continuous dosing regimen has been established in 2 placebo‑controlled trials in female patients ages 18 to 46 (Studies 8 and 9 [N=672]). Patients in these trials met DSM‑IV criteria for PMDD. Of 1,030 patients including Study 10, who were treated with daily doses of PAXIL CR 12.5 or 25 mg/day, or placebo continuously throughout the menstrual cycle for a period of 3 menstrual cycles, the mean duration of the PMDD symptoms was approximately 11 ± 7 years. Patients on systemic hormonal contraceptives were excluded from these trials. Therefore, the efficacy of PAXIL CR in combination with systemic (including oral) hormonal contraceptives for the continuous daily treatment of PMDD is unknown.

The VAS score is a patient‑rated instrument that mirrors the diagnostic criteria of PMDD as identified in the DSM‑IV, and includes assessments for mood, physical symptoms, and other symptoms associated with PMDD. In Studies 8 and 9, 12.5 mg/day and 25 mg/day of PAXIL CR were statistically significantly more effective than placebo as measured by change from baseline to Month 3 on the luteal phase VAS score.

In an additional study employing luteal phase dosing (Study 11), patients (N = 366) were treated for the 2 weeks prior to the onset of menses with 12.5 or 25 mg/day of PAXIL CR or placebo for a period of 3 months. In this trial,12.5 mg/day and 25 mg/day of PAXIL CR, as luteal phase dosing, was statistically significantly more effective than placebo as measured by change from baseline to luteal phase VAS score at Month 3.

There is insufficient information to determine the effect of race or age on outcome in Studies 8, 9, 10, and 11.

16 HOW SUPPLIED/STORAGE AND HANDLING

PAXIL CR is supplied as a round extended-release tablet, as follows:

12.5 mg yellow tablets

NDC 60505-4377-3 Bottles of 30 (one face is plain and the other is engraved with 12.5)

25 mg pink tablets

NDC 60505-4378-3 Bottles of 30 (one face is plain and the other is engraved with 25)

37.5 mg blue tablets

NDC 60505-4379-3 Bottles of 30 (one face is plain and the other is engraved with 37.5)

Store at or below 20° to 25°C (68° to 77°F); excursions permitted between 15° to 30°C (59° to 30°F [see USP Controlled Room Temperature].

17 PATIENT COUNSELING INFORMATION

Advise the patient to read the FDA-approved patient labeling (Medication Guide).

Suicidal Thoughts and Behaviors

Advise patients and caregivers to look for the emergence of suicidality, especially early during treatment and when the dosage is adjusted up or down, and instruct them to report such symptoms to the healthcare provider [see Boxed Warning and Warnings and Precautions (5.1)].

Important Administration Instructions

Instruct patients to swallow PAXIL CR whole and to not chew or crush the tablets [see Dosage and Administration (2.1)].

Serotonin Syndrome

Caution patients about the risk of serotonin syndrome, particularly with the concomitant use of PAXIL CR with other serotonergic drugs including triptans, tricyclic antidepressants, opioids, lithium, tryptophan, buspirone, amphetamines, St. John’s Wort, and with drugs that impair metabolism of serotonin (in particular, MAOIs, both those intended to treat psychiatric disorders and also others, such as linezolid). Instruct patients to contact their health care provider or report to the emergency room if they experience signs or symptoms of serotonin syndrome [see Warnings and Precautions (5.2), Drug Interactions (7.1)].

Concomitant Medications

Advise patients to inform their physician if they are taking, or plan to take, any prescription or over‑the‑counter drugs, since there is a potential for drug-drug interactions [see Warning and Precautions (5.3), Drug Interactions (7)].

Increased Risk of Bleeding

Inform patients about the concomitant use of PAXIL CR with aspirin, NSAIDs, other antiplatelet drugs, warfarin, or other anticoagulants because the combined use has been associated with an increased risk of bleeding. Advise patients to inform their health care providers if they are taking or planning to take any prescription or over-the counter medications that increase the risk of bleeding [see Warnings and Precautions (5.5)].

Activation of Mania/Hypomania

Advise patients and their caregivers to observe for signs of activation of mania/hypomania and instruct them to report such symptoms to the healthcare provider [see Warnings and Precautions (5.6)].

Discontinuation Syndrome

Advise patients not to abruptly discontinue PAXIL CR and to discuss any tapering regimen with their healthcare provider. Inform patients that adverse reactions can occur when PAXIL CR is discontinued [See Warnings and Precautions (5.7)].

Sexual Dysfunction

Advise patients that use of PAXIL CR may cause symptoms of sexual dysfunction in both male and female patients. Inform patients that they should discuss any changes in sexual function and potential management strategies with their healthcare provider [see Warnings and Precautions (5.13)].

Embryo-Fetal Toxicity

Advise women to notify their healthcare provider if they become pregnant or intend to become pregnant during treatment with PAXIL CR. Advise women of risks associated with first trimester use of PAXIL CR and that use later in pregnancy may lead to an increased risk for neonatal complications requiring prolonged hospitalization, respiratory support, tube feeding, and/or persistent pulmonary hypertension of the newborn (PPHN) [see Warnings and Precautions (5.4), Use in Specific Populations (8.1)]. Advise women that there is a pregnancy exposure registry that monitors pregnancy outcomes in women exposed to PAXIL CR during pregnancy [see Warnings and Precautions (5.4), Use in Specific Populations (8.1)].

Lactation

Advise breastfeeding women using PAXIL CR to monitor infants for agitation, irritability, poor feeding and poor weight gain and to seek medical care if they notice these signs [see Use in Specific Populations (8.2)].

Females and Males of Reproductive Potential

Advise men that PAXIL CR may affect sperm quality, which may impair fertility; it is unknown if this effect is reversible [see Use in Specific Populations (8.3)].

Allergic Reactions

Advise patients to notify their healthcare provider if they develop an allergic reaction such as rash, hives, swelling, or difficulty breathing [see Adverse Reactions (6.1, 6.2)].

Manufactured by:

Apotex Inc.

Toronto, Ontario

M9L 1T9

Manufactured for:

Apotex Corp.

Weston FL 33326

All registered trademarks in this document are the property of their respective owners.

MEDICATION GUIDE

PAXIL CR® (PAX-il) (paroxetine hydrochloride) extended-release tablets

What is the most important information I should know about PAXIL CR?

PAXIL CR can cause serious side effects, including:

- Increased risk of suicidal thoughts or actions. Antidepressant medicines may increase suicidal thoughts and actions in some children and young adults within the first few months of treatment or when the dose is changed. PAXIL CR is not for use in people younger than 18 years of age.

How can I watch for and try to prevent suicidal thoughts and actions?

- Depression or other serious mental illnesses are the most important causes of suicidal thoughts and actions.
- Pay close attention to any changes, especially sudden changes in mood, behavior, thoughts or feelings or if you develop suicidal thoughts or actions. This is very important when an antidepressant medicine is started or when the dose is changed.
- Call your healthcare provider right away to report new or sudden changes in mood, behavior, thoughts or feelings or if you develop suicidal thoughts or actions.
- Keep all follow-up visits with your healthcare provider as scheduled. Call your healthcare provider between visits as needed, especially if you have concerns about symptoms.

Call your healthcare provider or get emergency medical help right away if you have any of the following symptoms, especially if they are new, worse, or worry you:

- attempts to commit suicide
- acting aggressive or violent
- new or worse depression
- feeling agitated, restless, angry, or irritable
- an increase in activity and talking more than what is normal for you
- acting on dangerous impulses
- thoughts about suicide or dying
- new or worse anxiety or panic attacks
- trouble sleeping
- other unusual changes in behavior or mood

What is PAXIL CR?

PAXIL CR is a prescription medicine used in adults to treat:

- A certain type of depression called Major Depressive Disorder (MDD)
- Panic Disorder
- Social Anxiety Disorder (SAD)
- Premenstrual Dysphoric Disorder (PMDD)

Do not take PAXIL CR if you:

- take a monoamine oxidase inhibitor (MAOI)
- have stopped taking an MAOI in the last 14 days
- are being treated with the antibiotic linezolid or intravenous methylene blue
- are taking thioridazine
- are taking pimozide
- are allergic to paroxetine or any of the ingredients in PAXIL CR. See the end of this Medication Guide for a complete list of ingredients in PAXIL CR.

Ask your healthcare provider or pharmacist if you are not sure if you take an MAOI or one of these medicines, including intravenous methylene blue.

Do not start taking an MAOI for at least 14 days after you stop treatment with PAXIL CR.

Before taking PAXIL CR, tell your healthcare provider about all your medical conditions, including if you:

- have heart problems
- have or had bleeding problems
- have, or have a family history of bipolar disorder, mania or hypomania
- have or had seizures or convulsions
- have glaucoma (high pressure in the eye)
- have low sodium levels in your blood
- have bone problems
- have kidney or liver problems
- are pregnant or plan to become pregnant. PAXIL CR may harm your unborn baby.
  - Taking PAXIL CR during your first trimester of pregnancy may cause your baby to be at an increased risk of having a heart problem (cardiac malformations) at birth.
  - Taking PAXIL CR during your third trimester of pregnancy may cause your baby to have breathing,temperature, and feeding problems, low muscle tone (floppy baby syndrome), and irritability after birth and may cause your baby to be at an increased risk of a serious lung problem at birth. Talk to your healthcare provider about the risk to your unborn baby if you take PAXIL CR during pregnancy.
  - Tell your healthcare provider right away if you become pregnant or think you are pregnant during treatment with PAXIL CR.
  - There is a pregnancy registry for females who are exposed to PAXIL CR during pregnancy. The purpose ofthe registry is to collect information about the health of females exposed to PAXIL CR and their baby. Ifyou become pregnant during treatment with PAXIL CR talk to your healthcare provider about registeringwith the National Pregnancy Registry for Antidepressants at 1-866-961-2388 or visit online at https://womensmentalhealth.org/clinical-and-research-programs/pregnancyregistry/antidepressants/.
- are breastfeeding or plan to breastfeed. PAXIL CR passes into your breast milk. Talk to your healthcare provider about the best way to feed your baby during treatment with PAXIL CR.

Tell your healthcare provider about all the medicines you take, including prescription and over-the-counter medicines, vitamins, and herbal supplements.

PAXIL CR and some other medicines may affect each other causing possible serious side effects. PAXIL CR may affect the way other medicines work and other medicines may affect the way PAXIL CR works.

Especially tell your healthcare provider if you take:

- medicines used to treat migraine headaches called triptans
- tricyclic antidepressants
- lithium
- tramadol, fentanyl, meperidine, methadone, or other opioids
- tryptophan
- buspirone
- amphetamines
- St. John’s Wort
- medicines that can affect blood clotting such as aspirin, nonsteroidal anti-inflammatory drugs (NSAIDs), or warfarin
- diuretics
- tamoxifen

Ask your healthcare provider if you are not sure if you are taking any of these medicines. Your healthcare provider can tell you if it is safe to take PAXIL CR with your other medicines.

Do not start or stop any other medicines during treatment with PAXIL CR without talking to your healthcare provider first. Stopping PAXIL CR suddenly may cause you to have serious side effects. See, “What are the possible side effects of PAXIL CR?”

Know the medicines you take. Keep a list of them to show to your healthcare provider and pharmacist when you get a new medicine.

How should I take PAXIL CR?

- Take PAXIL CR exactly as your healthcare provider tell you to. Your healthcare provider may need to change the dose of PAXIL CR until it is the right dose for you.
- Take PAXIL CR 1 time each day in the morning.
- Take PAXIL CR with or without food.
- Swallow PAXIL CR tablets whole. Do not chew or crush PAXIL CR tablets.
- If you take too much PAXIL CR, call your poison control center at 1-800-222-1222 or got to the nearest hospital emergency room right away.

What are possible side effects of PAXIL CR?

PAXIL CR may cause serious side effects, including:

- See, “What is the most important information I should know about PAXIL CR?”
- Serotonin syndrome. A potentially life-threatening problem called serotonin syndrome can happen when you take PAXIL CR with certain other medicines. See, “Who should not take PAXIL CR?” Call your healthcare provider or go to the nearest hospital emergency room right away if you have any of the following signs and symptoms of serotonin syndrome:

- agitation
- seeing or hearing things that are not real (hallucinations)
- confusion
- coma
- fast heart beat
- changes in blood pressure
- dizziness
- sweating
- flushing
- high body temperature (hyperthermia)
- shaking (tremors), stiff muscles, or muscle twitching
- loss of coordination
- seizures
- nausea, vomiting, diarrhea

- Medicine interactions. Taking PAXIL CR with certain other medicines including thioridazine and pimozide may increase the risk of developing a serious heart problem called QT prolongation.
- Abnormal bleeding. Taking PAXIL CR with aspirin, NSAIDs, or blood thinners may add to this risk. Tell your healthcare provider about any unusual bleeding or bruising.
- Manic episodes. Manic episodes may happen in people with bipolar disorder who take PAXIL CR. Symptoms may include:

- greatly increased energy
- racing thoughts
- unusually grand ideas
- talking more or faster than usual
- severe problems sleeping
- reckless behavior
- excessive happiness or irritability

- Discontinuation syndrome. Suddenly stopping PAXIL CR may cause you to have serious side effects. Your healthcare provider may want to decrease your dose slowly. Symptoms may include:

- nausea
- sweating
- changes in mood
- irritability and agitation
- dizziness
- electric shock feeling (paresthesia)
- tremor
- anxiety
- confusion
- headache
- tiredness
- problems sleeping
- ringing in your ears (tinnitus)
- seizures

- Seizures (convulsions).
- Eye problems (angle-closure glaucoma). PAXIL CR may cause a type of eye problem called angle-closure glaucoma in people with certain other eye conditions. You may want to undergo an eye examination to see if you are at risk and receive preventative treatment if you are.
- Low sodium levels in your blood (hyponatremia). Low sodium levels in your blood that may be serious and may cause death, can happen during treatment with PAXIL CR. Elderly people and people who take certain medicines may be at a greater risk for developing low sodium levels in your blood. Signs and symptoms may include:

- headache
- difficulty concentrating
- memory changes
- confusion
- weakness and unsteadiness on your feet which can lead to falls

In more severe or more sudden cases, signs and symptoms include:

- seeing or hearing things that are not real (hallucinations)
- fainting
- seizures
- coma
- stopping breathing (respiratory arrest)

- Bone fractures.
- Sexual problems (dysfunction). Taking selective serotonin reuptake inhibitors (SSRIs), including PAXIL CR, may cause sexual problems.
  Symptoms in males may include:
  - Delayed ejaculation or inability to have an ejaculation
  - Decreased sex drive
  - Problems getting or keeping an erection
  Symptoms in females may include:
  - Decreased sex drive
  - Delayed orgasm or inability to have an orgasm

Talk to your healthcare provider if you develop any changes in your sexual function or if you have any questions or concerns about sexual problems during treatment with PAXIL CR. There may be treatments your healthcare provider can suggest.

The most common side effects PAXIL CR include:

- male and female sexual function problems
- blurred vision
- weakness (asthenia)
- constipation
- decreased appetite
- diarrhea
- dizziness
- dry mouth
- problems sleeping
- nausea
- sleepiness
- sweating
- tremor

These are not all the possible side effects of PAXIL CR.

Call your doctor for medical advice about side effects. You may report side effects to FDA at 1-800-FDA-1088.

How should I store PAXIL CR?

- Store PAXIL CR at room temperature between 68°F to 77°F (20°C to 25°C).

Keep PAXIL CR and all medicines out of the reach of children.

General information about the safe and effective use of PAXIL CR.

Medicines are sometimes prescribed for purposes other than those listed in a Medication Guide. Do not take PAXIL CR for a condition for which it was not prescribed. Do not give PAXIL CR to other people, even if they have the same symptoms that you have. It may harm them. You may ask your healthcare provider or pharmacist for information about PAXIL CR that is written for healthcare professionals.

What are the ingredients in PAXIL CR?

Active ingredient: paroxetine hydrochloride

Inactive ingredients: glyceryl behenate, hypromellose, lactose monohydrate, magnesium stearate, methacrylic acid copolymer type C, polyethylene glycols, polysorbate 80, polyvinylpyrrolidone, silicon dioxide, sodium lauryl sulfate, talc, titanium dioxide, triethyl citrate and the following colorants: D&C Red No. 30 aluminum lake (25 mg), D&C Yellow No. 10 aluminum lake (12.5 mg), FD&C Blue No. 2 aluminum lake (37.5 mg), FD&C Yellow No. 6 aluminum lake (12.5 mg), red ferric oxide (25 mg) and Yellow ferric oxide (12.5 mg and 37.5 mg).

All registered trademarks in this document are the property of their respective owners.

This Medication Guide has been approved by the U.S. Food and Drug Administration.

Manufactured by:

Apotex Inc.

Toronto, Ontario

M9L 1T9

Manufactured for:

Apotex Corp.

Weston, FL 33326

For more information about PAXIL CR call 1-800-706-5575.

This Medication Guide has been approved by the U.S. Food and Drug Administration.

01/2024

PACKAGE LABEL

Principal Display Panel

Representative sample of labeling (see HOW SUPPLIED section for complete listing):

APOTEX CORP. NDC 60505-4377-3

PAXIL CR®

PAROXETINE HCl

CONTROLLED-RELEASE TABLETS

12.5 mg

30 Tablets

Rx only

PACKAGE LABEL

Principal Display Panel

Representative sample of labeling (see HOW SUPPLIED section for complete listing):

APOTEX CORP. NDC 60505-4378-3

PAXIL CR®

PAROXETINE HCl

CONTROLLED-RELEASE TABLETS

25 mg

30 Tablets

Rx only

PACKAGE LABEL

Principal Display Panel

Representative sample of labeling (see HOW SUPPLIED section for complte listing):

APOTEX CORP. NDC 60505-4379-3

PAXIL CR®

PAROXETINE HCl

CONTROLLED-RELEASE TABLETS

37.5 mg

30 Tablets

Rx only

PACKAGE LABEL

Principal Display Panel

NDC 60505-3668-3

PAXIL CR®

PAROXETINE HCl

CONTROLLED-RELEASE TABLETS

12.5 mg

30 tablets

Rx only

Federal Law requires dispensing of Paxil CR® with the Medication Guide provided with this bottle.

Store at or below 25°C (77°F) [see USP].

Each controlled-release tablet contains paroxetine hydrochloride equivalent to 12.5 mg paroxetine.

Dosage: See accompanying prescribing information.

Important: Use safety closures when dispensing this product unless otherwise directed by physician or requested by purchaser.

Manufactured by:

GlaxoSmithKline

RTP, NC 27709

Distributed by:

Apotex Corp.

Weston, FL 33326

Made in Canada

PACKAGE LABEL

Principal Display Panel

NDC 60505-3669-3

PAXIL CR®

PAROXETINE HCl

CONTROLLED-RELEASE TABLETS

25 mg

30 tablets

Rx only

Federal Law requires dispensing of Paxil CR® with the Medication Guide provided with this bottle.

Store at or below 25°C (77°F) [see USP].

Each controlled-release tablet contains paroxetine hydrochloride equivalent to 25 mg paroxetine.

Dosage: See accompanying prescribing information.

Important: Use safety closures when dispensing this product unless otherwise directed by physician or requested by purchaser.

Manufactured by:

GlaxoSmithKline

RTP, NC 27709

Distributed by:

Apotex Corp.

Weston, FL 33326

Made in Canada

PACKAGE LABEL

Principal Display Panel

NDC 60505-3670-3

PAXIL CR®

PAROXETINE HCl

CONTROLLED-RELEASE TABLETS

37.5 mg

30 tablets

Rx only

Federal Law requires dispensing of Paxil CR® with the Medication Guide provided with this bottle.

Store at or below 25°C (77°F) [see USP].

Each controlled-release tablet contains paroxetine hydrochloride equivalent to 37.5 mg paroxetine.

Dosage: See accompanying prescribing information.

Important: Use safety closures when dispensing this product unless otherwise directed by physician or requested by purchaser.

Manufactured by:

GlaxoSmithKline

RTP, NC 27709

Distributed by:

Apotex Corp.

Weston, FL 33326

Made in Canada